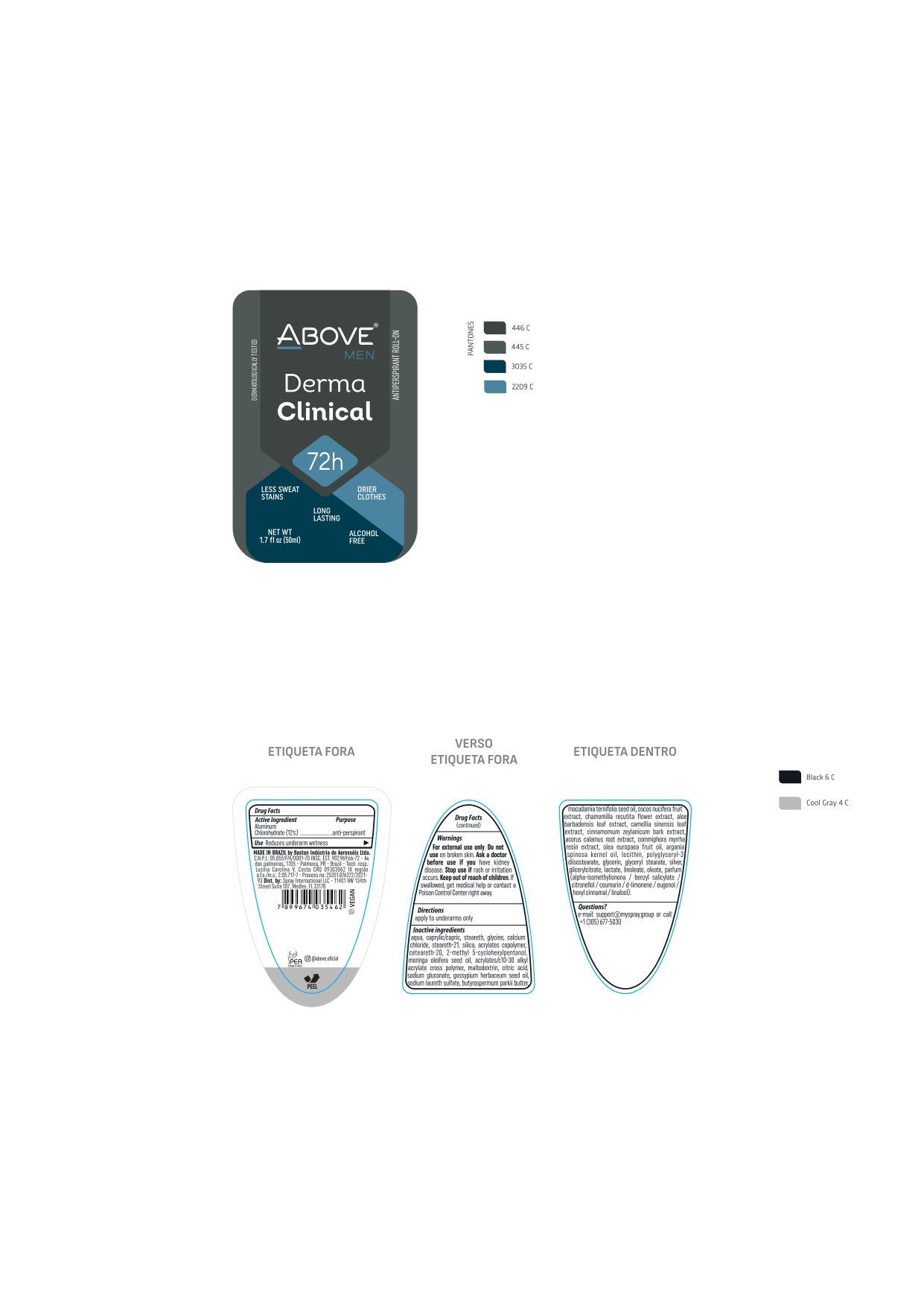 DRUG LABEL: Above Dermaclinical  Men 72 hours
NDC: 73306-1137 | Form: CREAM
Manufacturer: BASTON INDUSTRIA DE AEROSSOIS LTDA
Category: otc | Type: HUMAN OTC DRUG LABEL
Date: 20241226

ACTIVE INGREDIENTS: ALUMINUM CHLOROHYDRATE 12 mg/100 g
INACTIVE INGREDIENTS: MEDIUM-CHAIN TRIGLYCERIDES

ABOVE DERMACLINICAL MEN 72 H

INACTIVE INGREDIENT

AQUA
CAPRYLIC/CAPRIC TRIGLYCERIDE
STEARETH 2
GLYCINE
CALCIUM CHLORIDE
STEARETH-21
PARFUM
SILICA
ACRYLATES COPOLYMER
CETEARETH-20
2-METHYL 5-CYCLOHEXYLPENTANOL
MORINGA OLEIFERA SEED OIL
ACRYLATES / C10-30 ALKYL ACRYLATE CROSS POLYMER
MALTODEXTRIN
CITRIC ACID
SODIUM GLUCONATE
GOSSYPIUM HERBACEUM SEED OIL
SODIUM LAURETH SULFATE
BUTYROSPERMUM PARKII BUTTER
MACADAMIA TERNIFOLIA SEED OIL
COCOS NUCIFERA FRUIT EXTRACT
CHAMOMILLA RECUTITA FLOWER EXTRACT
ALOE BARBADENSIS LEAF EXTRACT
CAMELLIA SINENSIS LEAF EXTRACT
CINNAMOMUM ZEYLANICUM BARK EXTRACT
ACORUS CALAMUS ROOT EXTRACT
COMMIPHORA MYRRHA RESIN EXTRACT
OLEA EUROPAEA FRUIT OIL
ARGANIA SPINOSA KERNEL OIL
LECITHIN
POLYGLYCERYL-3 DIISOSTEARATE
GLYCERIN
GLYCERYL STEARATE
SILVER
GLICERYLCITRATE / LACTATE / LINOLEATE / OLEATE

WARNING SECTION

FOR EXTERNAL USE ONLY . DO NOT USE ON BROKEN SKIN